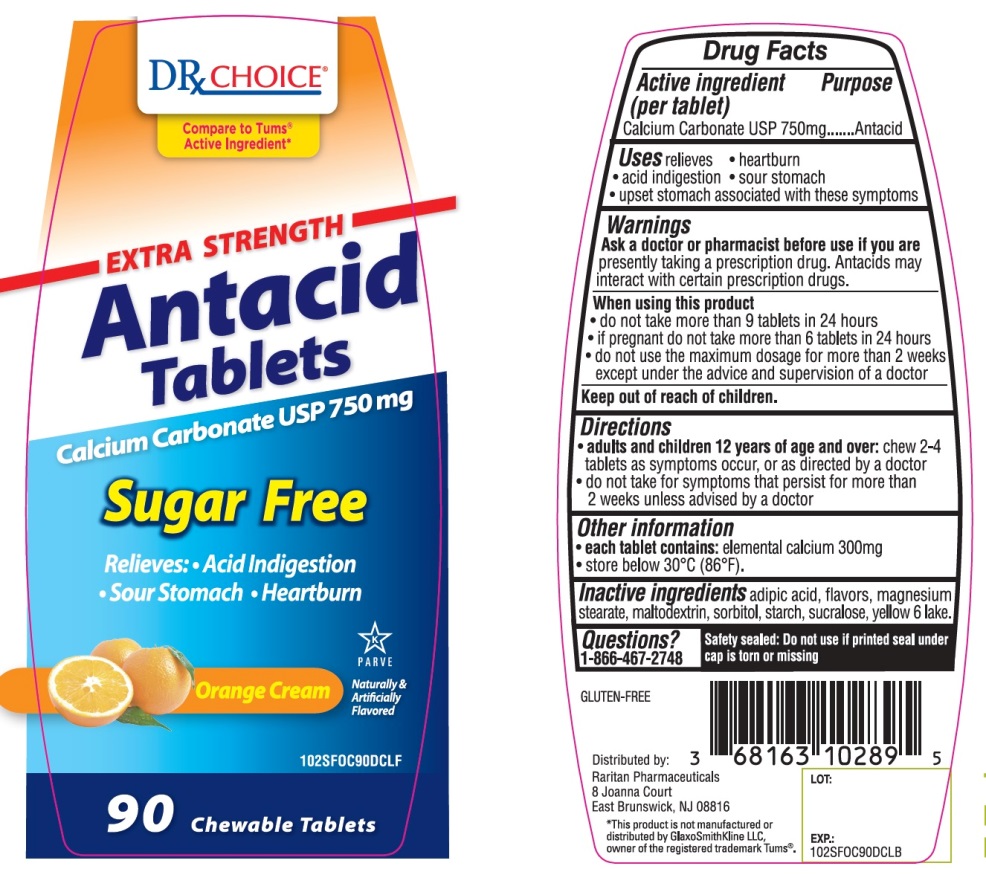 DRUG LABEL: Extra Strength Sugar Free
NDC: 68163-202 | Form: TABLET, CHEWABLE
Manufacturer: Raritan Pharmaceuticals Inc
Category: otc | Type: HUMAN OTC DRUG LABEL
Date: 20220114

ACTIVE INGREDIENTS: CALCIUM CARBONATE 750 mg/1 1
INACTIVE INGREDIENTS: ADIPIC ACID; MAGNESIUM STEARATE; MALTODEXTRIN; SORBITOL; STARCH, CORN; SUCRALOSE; FD&C YELLOW NO. 6

Extra Strength SUGAR FREE Antacid Tablets Calcium Carbonate 750 mg

Active ingredient (per tablet)

Calcium Carbonate USP 750 mg

Purpose

Antacid

Uses

relieves

- heartburn
- acid indigestion
- sour stomach
- upset stomach associated with these symptoms

Warnings

Ask a doctor or pharmacist before use if you are presently taking a prescription drug. Antacids may interact with certain prescription drugs.

When using this product

- do not take more than 9 tablets in 24 hours
- If pregnant do not take more than 6 tablets in 24 hours
- do not use the maximum dosage for more than 2 weeks except under the advice and supervision of a doctor

Directions

- adults and children 12 years of age and over: chew 2-4 tablets as symptoms occur ,or as directed by a doctor
- do not take for symptoms that persist for more than 2 weeks unless advised by a doctor

Other Information

- each tablet contains: elemental calcium 300 mg
- store below 30°C (86°F).

Inactive ingredients

adipic acid, flavors, magnesium stearate, maltodextrin, sorbitol, starch, sucralose, FD&C Yellow No. 6 lake.

Questions or comments?

1-866-467-2748

SAFETY SEALED: DO NOT USE IF PRINTED SEAL UNDER CAP IS TORN OR MISSING

Package/Label Principal Display Panel

NDC 68163-202-90

DRxCHOICE®

Compare to Tums® active ingredient*

EXTRA STRENGTH

Antacid

Tablets

Calcium Carbonate USP 750 mg

Sugar-Free

Relieves:

- Acid Indigestion
- Sour Stomach

90 CHEWABLE TABLETS

K PARVE

Distributed by:

Raritan Pharmaceuticals

8 Joanna Court, East Brunswick, NJ 08816

*This product is not manufactured or distributed by GlaxoSmithKline LLC, owner of the registered trademark, TUMS®.